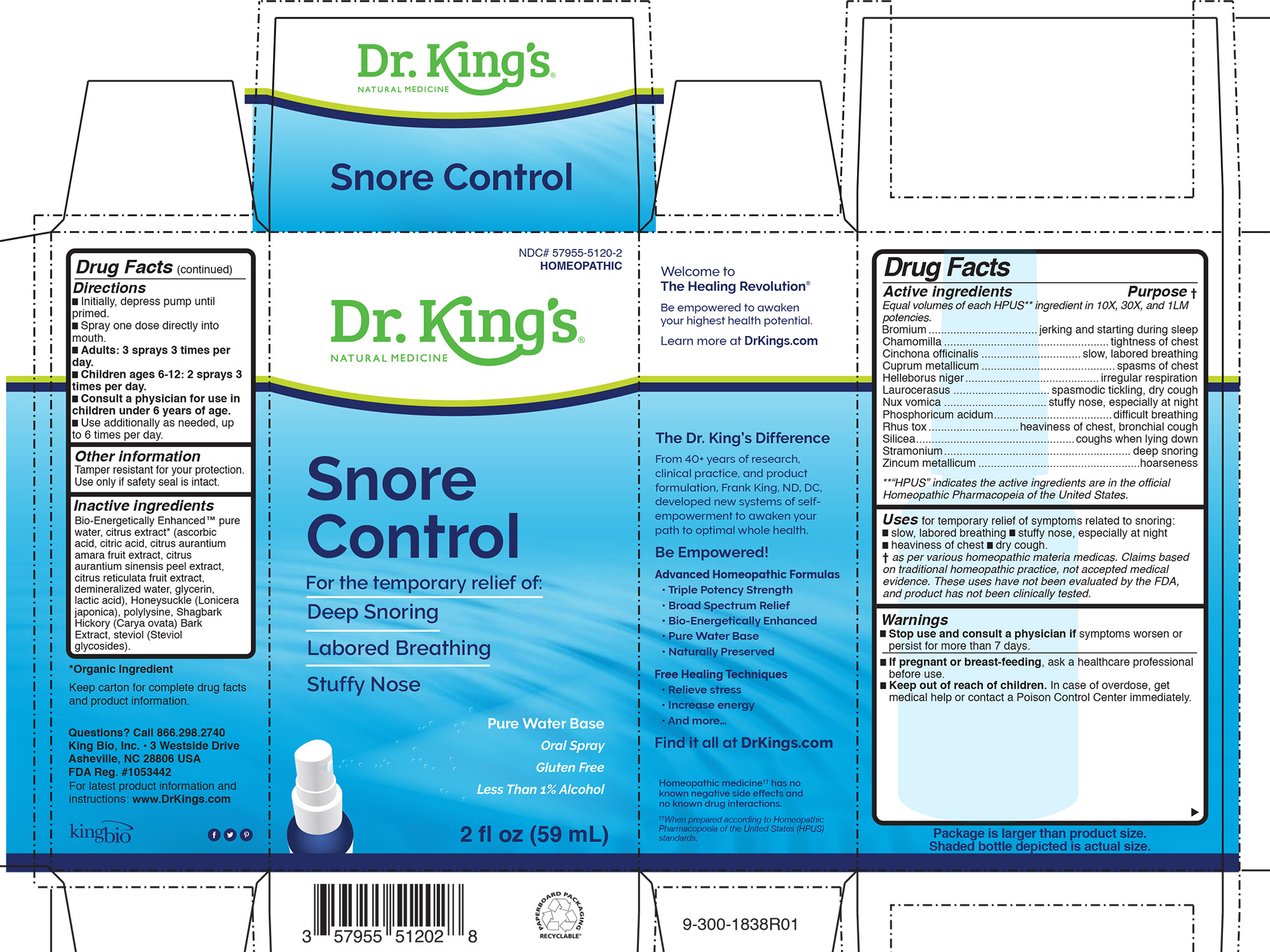 DRUG LABEL: Snore Control
NDC: 57955-5120 | Form: LIQUID
Manufacturer: King Bio Inc.
Category: homeopathic | Type: HUMAN OTC DRUG LABEL
Date: 20200902

ACTIVE INGREDIENTS: BROMINE 10 [hp_X]/59 mL; MATRICARIA CHAMOMILLA 10 [hp_X]/59 mL; CINCHONA OFFICINALIS BARK 10 [hp_X]/59 mL; COPPER 10 [hp_X]/59 mL; HELLEBORUS NIGER ROOT 10 [hp_X]/59 mL; PRUNUS LAUROCERASUS LEAF 10 [hp_X]/59 mL; STRYCHNOS NUX-VOMICA SEED 10 [hp_X]/59 mL; PHOSPHORIC ACID 10 [hp_X]/59 mL; TOXICODENDRON PUBESCENS LEAF 10 [hp_X]/59 mL; SILICON DIOXIDE 10 [hp_X]/59 mL; DATURA STRAMONIUM 10 [hp_X]/59 mL; ZINC 10 [hp_X]/59 mL
INACTIVE INGREDIENTS: WATER; CARYA OVATA BARK; CITRUS BIOFLAVONOIDS; LONICERA JAPONICA FLOWER; POLYEPSILON-LYSINE (4000 MW); REBAUDIOSIDE A

Snore Control™

HPUS active ingredients

Equal volumes of each ingredient in 10X, 30X, and 1LM potencies.

Bromium

Chamomilla

Cinchona officinalis

Cuprum metallicum

Helleborus niger

Laurocerasus

Nux vomica

Phosphoricum acidum

Rhus toxicodendron

Silicea

Stramonium

INDICATIONS AND USAGE

Uses for temporary relief of symptoms related to snoring:
█ slow, labored breathing █ stuffy nose, especially at night
█ heaviness of chest █ dry cough.
† as per various homeopathic materia medicas. Claims based
on traditional homeopathic practice, not accepted medical
evidence. These uses have not been evaluated by the FDA,
and product has not been clinically tested.

Warnings

█ Stop use and consult a physician if symptoms worsen or
persist for more than 7 days.

PREGNANCY OR BREAST FEEDING

If pregnant or breast-feeding, ask a healthcare professional
before use.If pregnant or breast-feeding, ask a healthcare professional
before use.

Keep out of reach of children. In case of overdose, get
medical help or contact a Poison Control Center immediately.

Directions:

- Initially, depress pump until primed.
- Spray one dose directly into mouth.
- Adults: 3 sprays 3 times per day.
- Children ages 6-12: 2 sprays 3 times per day.
- Consult a physician for use in children under 6 years of age.
- Use additionally as needed, up to 6 times per day.

Other information
Tamper resistant for your protection.
Use only if safety seal is intact.Other information
Tamper resistant for your protection.
Use only if safety seal is intact.

Questions? Call 866.298.2740
King Bio, Inc. • 3 Westside Drive
Asheville, NC 28806 USA
FDA Reg. #1053442

For latest product information and
instructions: www.DrKings.com

Inactive Ingredients:

Bio-Energetically Enhanced™ pure
water, citrus extract* (ascorbic
acid, citric acid, citrus aurantium
amara fruit extract, citrus
aurantium sinensis peel extract,
citrus reticulata fruit extract,
demineralized water, glycerin,
lactic acid), Honeysuckle (Lonicera
japonica), polylysine, Shagbark
Hickory (Carya ovata) Bark
Extract, steviol (Steviol
glycosides).

HPUS active Ingredients: Purpose:

Equal volumes of each HPUS** ingredient in 10X, 30X, and 1LM
potencies.
Bromium...................................jerking and starting during sleep
Chamomilla .....................................................tightness of chest
Cinchona officinalis ................................slow, labored breathing
Cuprum metallicum ...........................................spasms of chest
Helleborus niger...........................................irregular respiration
Laurocerasus ...............................spasmodic tickling, dry cough
Nux vomica .................................stuffy nose, especially at night
Phosphoricum acidum......................................difficult breathing
Rhus tox.............................heaviness of chest, bronchial cough
Silicea...................................................coughs when lying down
Stramonium............................................................ deep snoring
Zincum metallicum ....................................................hoarseness
**“HPUS” indicates the active ingredients are in the official
Homeopathic Pharmacopeia of the United States.